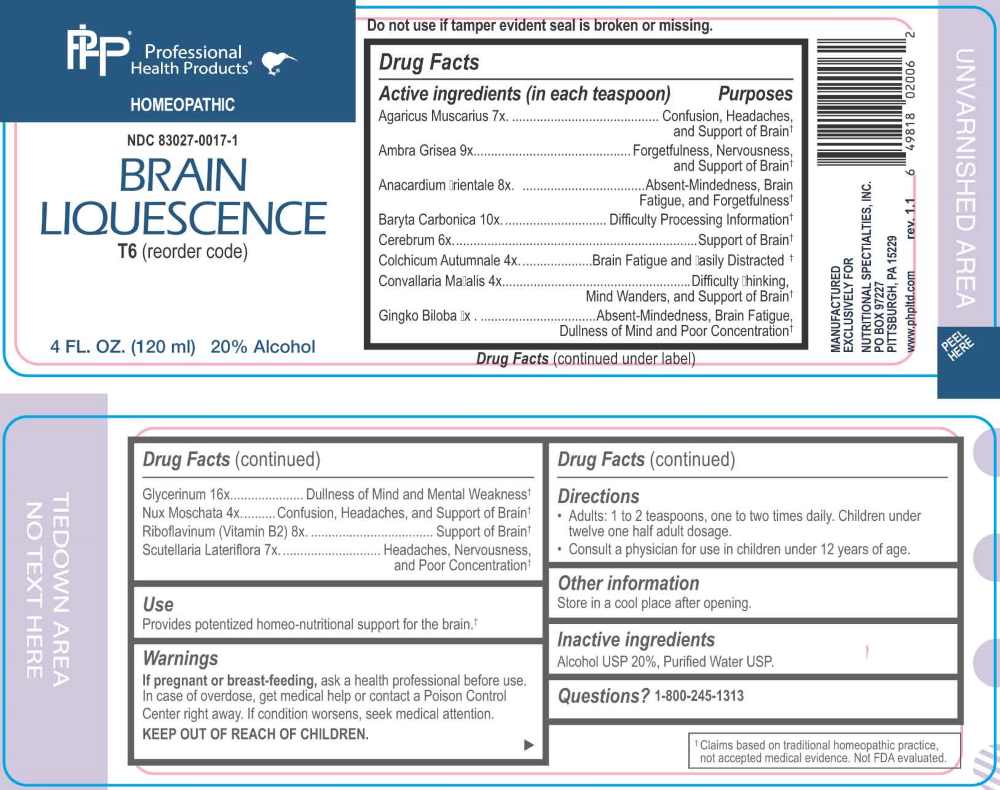 DRUG LABEL: Brain Liquescence
NDC: 83027-0017 | Form: LIQUID
Manufacturer: Nutritional Specialties, Inc.
Category: homeopathic | Type: HUMAN OTC DRUG LABEL
Date: 20251119

ACTIVE INGREDIENTS: GINKGO 3 [hp_X]/1 mL; COLCHICUM AUTUMNALE BULB 4 [hp_X]/1 mL; CONVALLARIA MAJALIS 4 [hp_X]/1 mL; NUTMEG 4 [hp_X]/1 mL; SUS SCROFA CEREBRUM 6 [hp_X]/1 mL; AMANITA MUSCARIA FRUITING BODY 7 [hp_X]/1 mL; SCUTELLARIA LATERIFLORA WHOLE 7 [hp_X]/1 mL; SEMECARPUS ANACARDIUM JUICE 8 [hp_X]/1 mL; RIBOFLAVIN 8 [hp_X]/1 mL; AMBERGRIS 9 [hp_X]/1 mL; BARIUM CARBONATE 10 [hp_X]/1 mL; GLYCERIN 16 [hp_X]/1 mL
INACTIVE INGREDIENTS: WATER; ALCOHOL

DRUG FACTS:

ACTIVE INGREDIENTS:

Agaricus Muscarius 7X, Ambra Grisea 9X, Anacardium Orientale 8X, Baryta Carbonica 10X, Cerebrum 6X, Colchicum Autumnale 4X, Convallaria Majalis 4X, Ginkgo Biloba 3X, Glycerinum 16X, Nux Moschata 4X, Riboflavinum (Vitamin B2) 8X, Scutellaria Lateriflora 7X.

PURPOSE:

Agaricus Muscarius – Confusion, Headaches, and Support of Brain,† Ambra Grisea – Forgetfulness, Nervousness, and Support of Brain,† Anacardium Orientale – Absent-Mindedness, Brain Fatigue, and Forgetfulness,† Baryta Carbonica – Difficulty Processing Information,† Cerebrum – Support of Brain,† Colchicum Autumnale – Brain Fatigue and Easily Distracted,† Convallaria Majalis – Difficulty Thinking, Mind Wanders, and Support of Brain,† Ginkgo Biloba – Absent-Mindedness, Brain Fatigue, Dullness of Mind and Poor Concentration,† Glycerinum – Dullness of Mind and Mental Weakness,† Nux Moschata – Confusion, Headaches, and Support of Brain,† Riboflavinum (Vitamin B2) – Support of Brain,† Scutellaria Lateriflora – Headaches, Nervousness, and Poor Concentration†

†Claims based on traditional homeopathic practice, not accepted medical evidence. Not FDA evaluated.

USES:

Provides potentized homeo-nutritional support for the brain.†

†Claims based on traditional homeopathic practice, not accepted medical evidence. Not FDA evaluated.

WARNINGS:

If pregnant or breast-feeding, ask a health professional before use.

In case of overdose, get medical help or contact a Poison Control Center right away.

If condition worsens, seek medical attention.

KEEP OUT OF REACH OF CHILDREN

Do not use if tamper evident seal is broken or missing.

Store in a cool place after opening

KEEP OUT OF REACH OF CHILDREN:

In case of overdose, get medical help or contact a Poison Control Center right away.

DIRECTIONS:

• Adults: 1 to 2 teaspoons, one to two times daily. Children under twelve one half adult dosage.

Consult a physician for use in children under 12 years of age.

INACTIVE INGREDIENTS:

Alcohol USP 20%, Purified Water USP.

QUESTIONS:

MANUFACTURED EXCLUSIVELY FOR

NUTRITIONAL SPECIALTIES, INC.

PO BOX 97227

PITTSBURG, PA 15229

www.phpltd.com

PACKAGE LABEL DISPLAY:

Professional

Health Products

HOMEOPATHIC

NDC 83027-0017-1

BRAIN LIQUESCENCE

4 FL. OZ (120 ml)